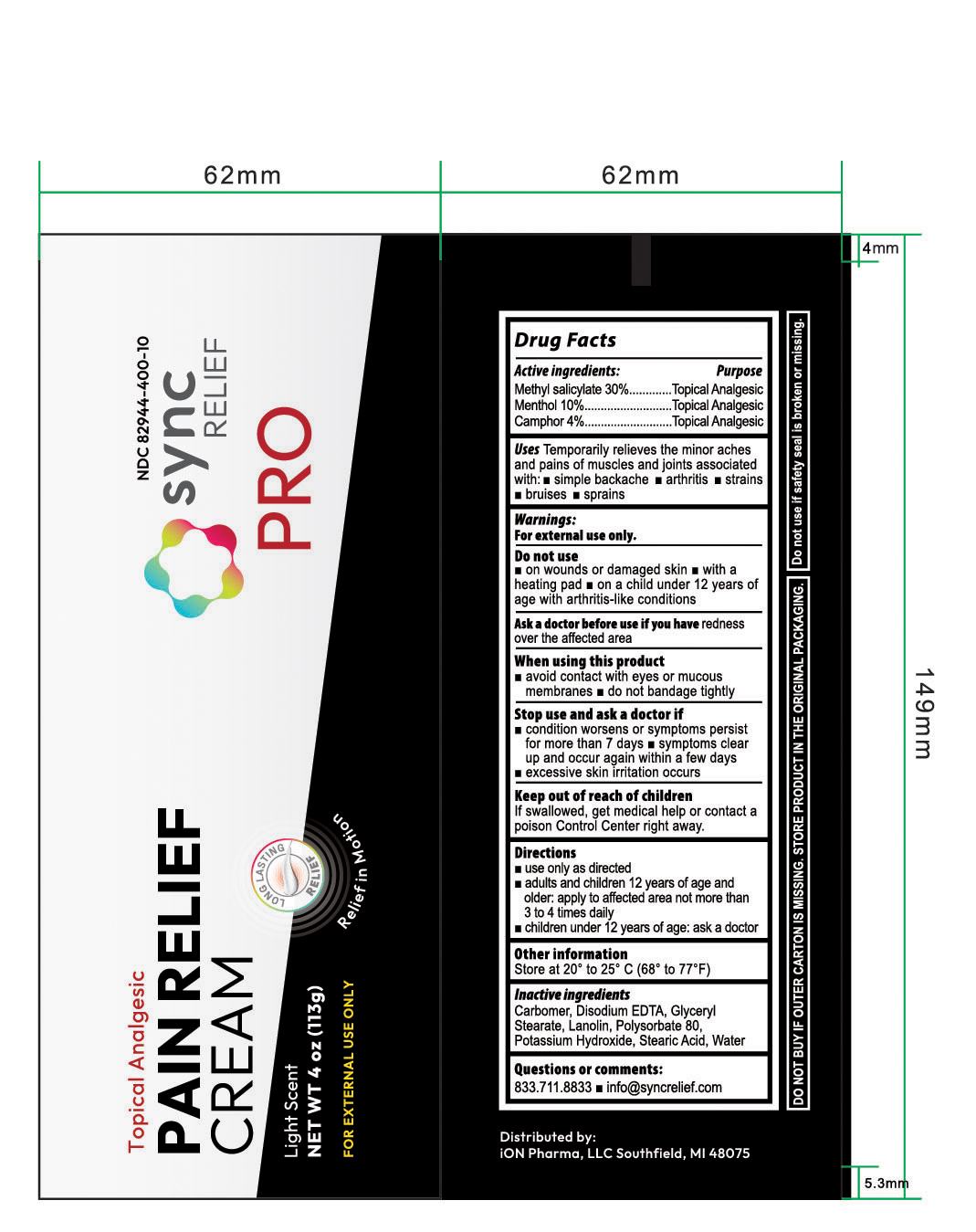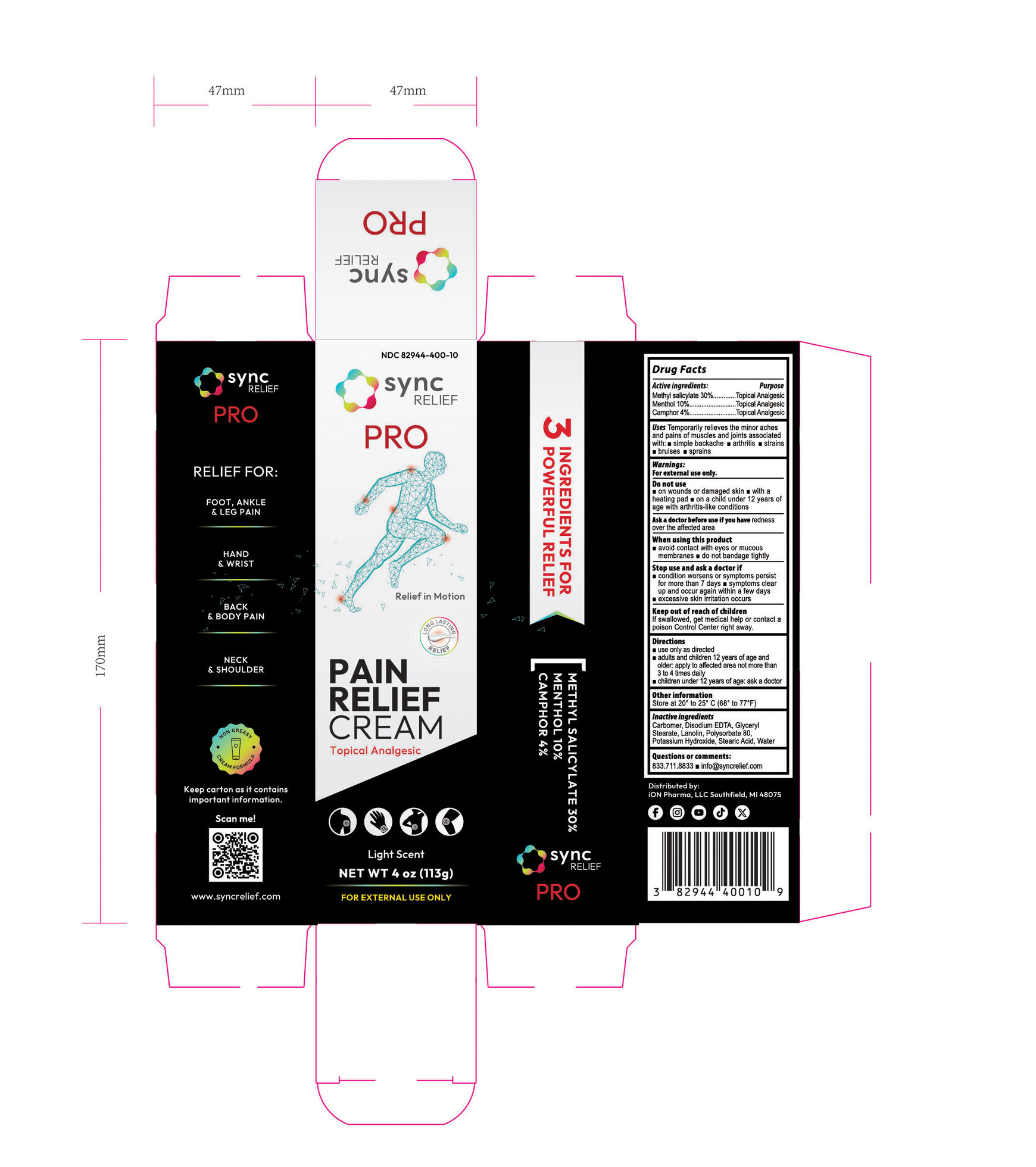 DRUG LABEL: SYNC PRO
NDC: 82944-400 | Form: CREAM
Manufacturer: iON Pharma, LLC
Category: otc | Type: HUMAN OTC DRUG LABEL
Date: 20250728

ACTIVE INGREDIENTS: METHYL SALICYLATE 30 g/1 1; CAMPHOR (SYNTHETIC) 4 g/1 1; MENTHOL 10 g/1 1
INACTIVE INGREDIENTS: EDETATE DISODIUM; POLYSORBATE 80; STEARIC ACID; POTASSIUM HYDROXIDE; LANOLIN; CARBOMER; WATER; GLYCERYL STEARATE

Sync Relief Pro Cream (Methyl salicylate 30%, Menthol 10%, Camphor 4%)

Drug facts active ingredients

Active ingredients: Purpose

Methyl salicylate 30%: Topical Analgesic

Menthol 10%: Topical Analgesic

Camphor 4%: Topical Analgesic

Uses

Uses Temporarily relieves the minor aches and pains of muscles and joints associated

with:

- simple backache
- arthritis
- strains
- bruises
- sprains

Do not use section

Do not use

- on wounds or damaged skin
- with a heating pad
- on a child under 12 years of age with arthritis-like conditions

When using this product section

When using this product

- avoid contact with eyes or mucous membranes
- do not bandage tightly

Stop use section

Stop use and ask a doctor if

- condition worsens or symptoms persist for more than 7 days
- symptoms clear up and occur again within a few days
- excessive skin irritation occurs

Keep out of reach of children section

Keep out of reach of children

If swallowed, get medical help or contact a Poison Control Center right away.

Directions section

Directions

- use only as directed
- adults and children 12 years of age and older: apply to affected area not more than 3 to 4 times daily
- children under 12 years of age: ask a doctor

Inactive ingredients

Carbomer, Disodium EDTA, Glyceryl Stearate, Lanolin, Polysorbate 80, Potassium Hydroxide, Stearic Acid, Water

Questions or comments section

Questions or comments:

833.711.8833

info@syncrelief.com

PACKAGE LABEL

NDC 82944-400-10

syn relief PRO

Relief in Motion

LONG LASTING RELIEF

PAIN RELIEF CREAM
Topical Analgesic

Light Scent

NET WT 4 oz (113 g)

FOR EXTERNAL USE ONLY